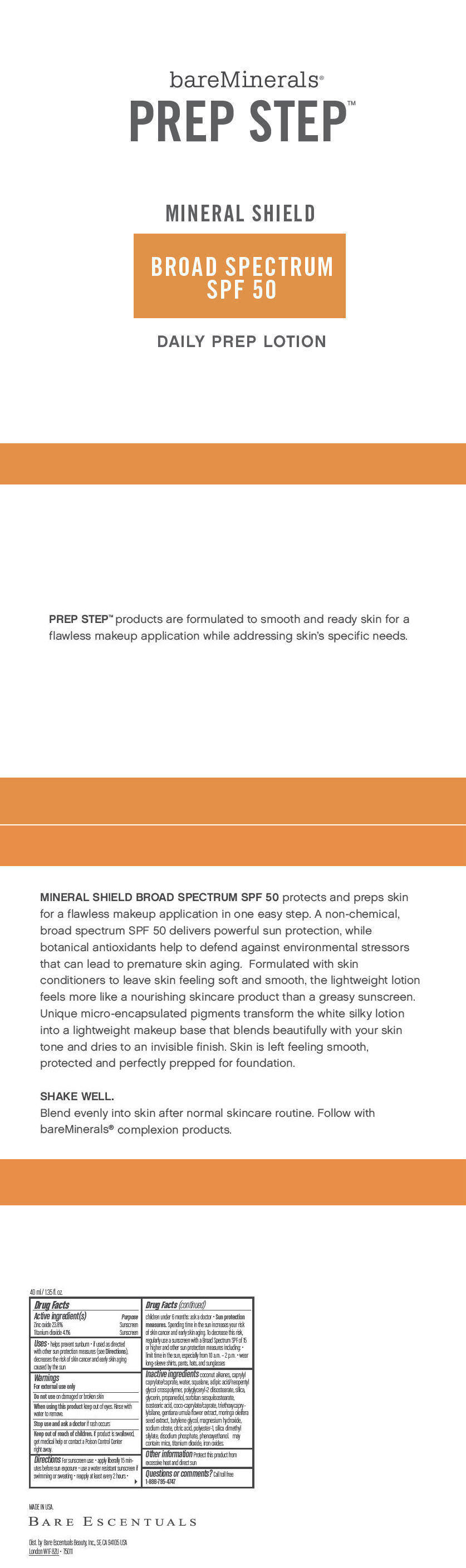 DRUG LABEL: bareMinerals Prep Step Mineral Shield Broad Spectrum SPF 50 Daily Prep
NDC: 98132-761 | Form: LOTION
Manufacturer: Bare Escentuals Beauty, Inc.
Category: otc | Type: HUMAN OTC DRUG LABEL
Date: 20150304

ACTIVE INGREDIENTS: Zinc Oxide 238 mg/1 mL; Titanium Dioxide 41 mg/1 mL
INACTIVE INGREDIENTS: coconut alkanes; caprylyl caprylate/caprate; water; squalene; polyglyceryl-2 diisostearate; silicon dioxide; glycerin; propanediol; isostearic acid; coco-caprylate/caprate; triethoxycaprylylsilane; gentiana urnula flower; moringa oleifera seed; butylene glycol; magnesium hydroxide; sodium citrate; citric acid monohydrate; silica dimethyl silylate; sodium phosphate, dibasic, anhydrous; phenoxyethanol; mica; ferric oxide red

bareMinerals® Prep Step™ Mineral Shield Broad Spectrum SPF 50 Daily Prep Lotion

Drug Facts

ACTIVE INGREDIENT

Active ingredient(s) | Purpose
Zinc oxide 23.8% | Sunscreen
Titanium dioxide 4.1% | Sunscreen

Uses

- helps prevent sunburn
- if used as directed with other sun protection measures (see Directions), decreases the risk of skin cancer and early skin aging caused by the sun

Warnings

For external use only

Do not use on damaged or broken skin

When using this product keep out of eyes. Rinse with water to remove.

Stop use and ask a doctor if rash occurs

Keep out of reach of children. If product is swallowed, get medical help or contact a Poison Control Center right away.

Directions

For sunscreen use:

- apply liberally 15 minutes before sun exposure
- use a water resistant sunscreen if swimming or sweating
- reapply at least every 2 hours
- children under 6 months: ask a doctor
- Sun protection measures. Spending time in the sun increases your risk of skin cancer and early skin aging. To decrease this risk, regularly use a sunscreen with a Broad Spectrum SPF of 15 or higher and other sun protection measures including:
  - limit time in the sun, especially from 10 a.m. – 2 p.m.
  - wear long-sleeve shirts, pants, hats, and sunglasses

Inactive ingredients

coconut alkanes, caprylyl caprylate/caprate, water, squalane, adipic acid/neopentyl glycol crosspolymer, polyglyceryl-2 diisostearate, silica, glycerin, propanediol, sorbitan sesquiisostearate, isostearic acid, coco-caprylate/caprate, triethoxycaprylylsilane, gentiana urnula flower extract, moringa oleifera seed extract, butylene glycol, magnesium hydroxide, sodium citrate, citric acid, polyester-1, silica dimethyl silylate, disodium phosphate, phenoxyethanol. may contain: mica, titanium dioxide, iron oxides.

Other information

Protect this product from excessive heat and direct sun

Questions or comments?

Call toll free 1-888-795-4747

Dist. by Bare Escentuals Beauty, Inc., SF, CA 94105 USA

PRINCIPAL DISPLAY PANEL - 40 mL Bottle Carton

bareMinerals®
PREP STEP™

MINERAL SHIELD

BROAD SPECTRUM
SPF 50

DAILY PREP LOTION